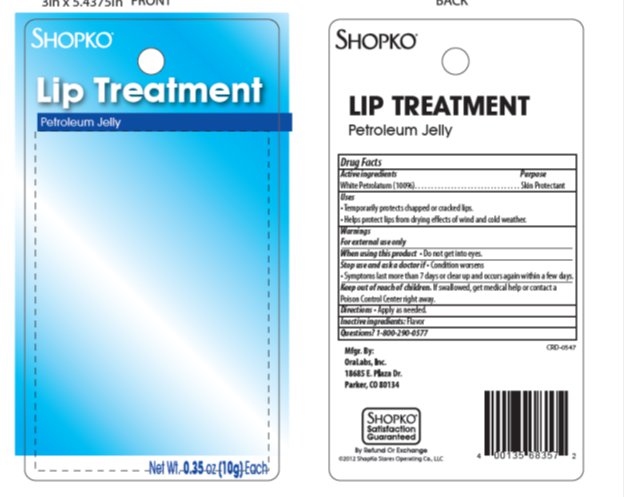 DRUG LABEL: Shopko Lip Treatment
NDC: 37012-736 | Form: GEL
Manufacturer: Shopko
Category: otc | Type: HUMAN OTC DRUG LABEL
Date: 20130724

ACTIVE INGREDIENTS: PETROLATUM 99.98 mg/1 g
INACTIVE INGREDIENTS: METHYL SALICYLATE 0.02 mg/1 g

Drug Facts

Active ingredient

Petrolatum, 100%

Purpose

Skin Protectant

Keep Out of Reach of Children

If swallowed, get medical help or contact a Poison Control Center right away.

Uses

Temporarily protects chapped or cracked lips. Helps protect lips from drying effects of wind and cold weather.

Warnings

For external use only. When using this product –Do not get into eyes. Stop use and ask a doctor if – condition worsens-symptoms last more than 7 days or clear up and occur again within a few days.

Directions

Apply as needed.

Inactive Ingredients

Flavor